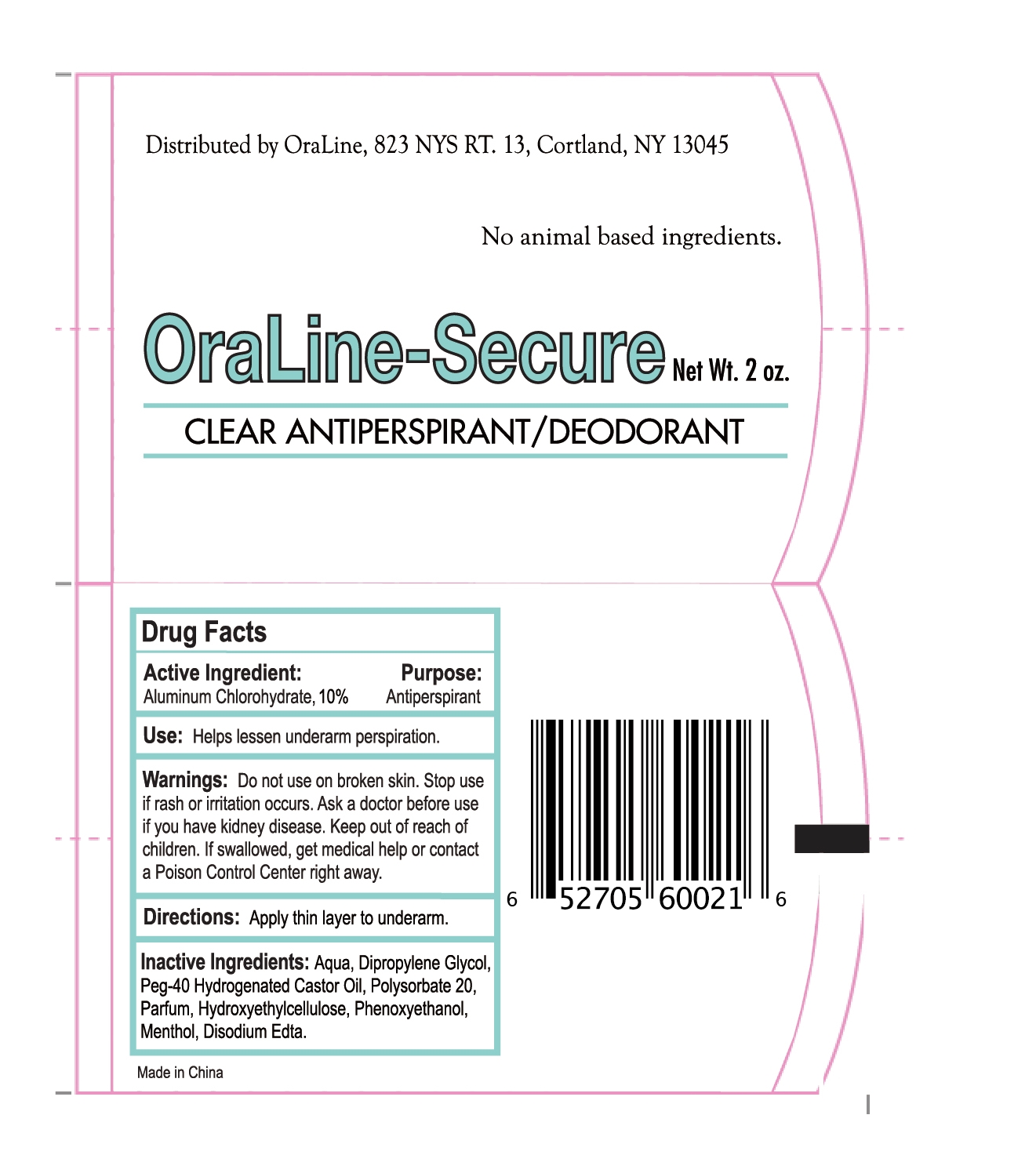 DRUG LABEL: aluminum chlorohydrate
NDC: 47993-331 | Form: GEL
Manufacturer: NINGBO JIANGBEI OCEAN STAR TRADING CO.,LTD
Category: otc | Type: HUMAN OTC DRUG LABEL
Date: 20221103

ACTIVE INGREDIENTS: ALUMINUM CHLOROHYDRATE 5.67 g/56.7 g
INACTIVE INGREDIENTS: WATER; DIPROPYLENE GLYCOL; POLYOXYL 40 HYDROGENATED CASTOR OIL; POLYSORBATE 20; HYDROXYETHYL CELLULOSE (2000 MPA.S AT 1%); PHENOXYETHANOL; MENTHOL; EDETATE DISODIUM

47993-331

Active ingredients
Aluminum Chlorohydrate, 10%

PURPOSE

Antiperspirant

Uses：

Helps lessen underarm perspiration.

Warnings:

Do not use on broken skin.

Stop use if rash or irritation occurs. Ask a doctor before use if you have kidney disease.

Keep out of reach of children. If swallowed, get medical help or contact a Poison Control Center right away.

Directions:

Apply thin layer to underarm.

Inactive Ingredients:

Aqua, Dipropylene Glycol, Peg-40 Hydrogenated Castor Oil, Polysorbate 20, Parfum, Hydroxyethylcellulose, Phenoxyethanol, Menthol, Disodium Edta.